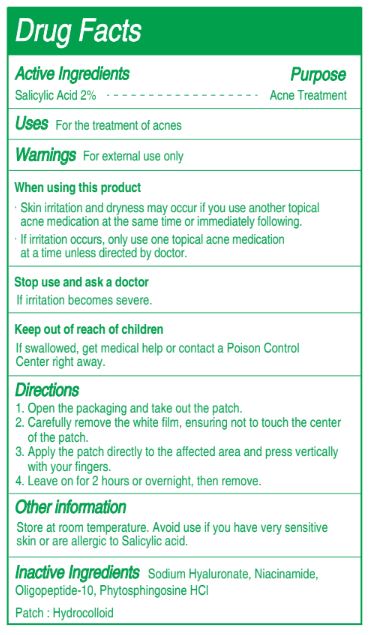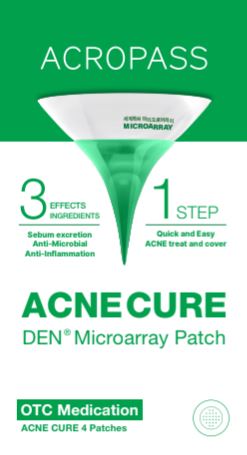 DRUG LABEL: ACROPASS ACNE CURE
NDC: 71134-241 | Form: PATCH
Manufacturer: RAPHAS CO., LTD
Category: otc | Type: HUMAN OTC DRUG LABEL
Date: 20240826

ACTIVE INGREDIENTS: SALICYLIC ACID 0.012 mg/0.6013 mg
INACTIVE INGREDIENTS: PHYTOSPHINGOSINE HYDROCHLORIDE; NIACINAMIDE; HYALURONATE SODIUM; OLIGOPEPTIDE-10

Active Ingredients Purpose

Salicylic Acid 2%.................................................... Acne Treatment

PURPOSE

Uses: For the treatment of acnes

WARNINGS

For external use only

WHEN USING

- Skin irritation and dryness may occur if you use another topical acne medication at the same time or immediately following.
- If irritation occurs, only use one topical acne medication at a time unless directed by doctor.

STOP USE

if irritation becomes severe.

ASK DOCTOR

if irritation becomes severe.

KEEP OUT OF REACH OF CHILDREN

if swallowed, get medical help or contact a Poison Control Center right away.

STORAGE AND HANDLING

Store at room temperature. Avoid use if you have very sensitive skin or anr allergic to Salicylic acid.

INACTIVE INGREDIENT

Sodium Hyaluronate, Niacinamide, Oligopeptide-10, Phytosphingosine HCl

Patch : Hydrocolloid

DOSAGE AND ADMINISTRATION

1. Open the packaging and take out the patch.
2. Carefully remove the white film, ensuring not to touch the center of the patch.
3. Apply the patch directly to the affected area and press vertically with your fingers.
4. Leave on for 2 hours or overnight, then remove.

INDICATIONS AND USAGE

1. Open the packaging and take out the patch.
2. Carefully remove the white film, ensuring not to touch the center of the patch.
3. Apply the patch directly to the affected area and press vertically with your fingers.
4. Leave on for 2 hours or overnight, then remove.